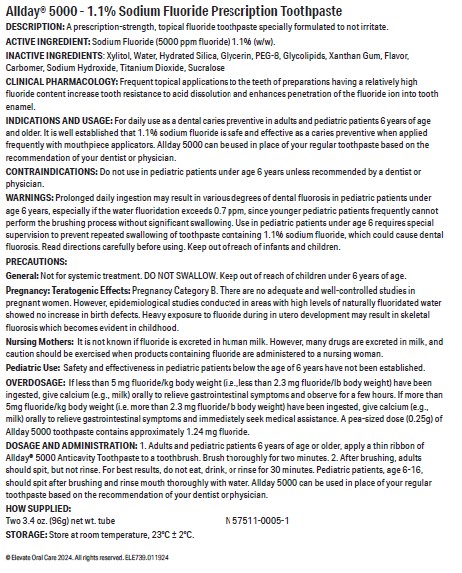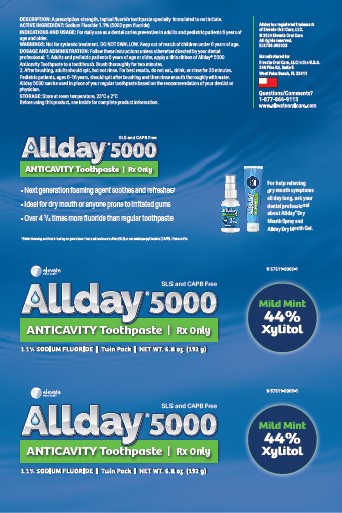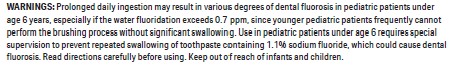 DRUG LABEL: Allday 5000
NDC: 57511-0005 | Form: PASTE, DENTIFRICE
Manufacturer: Elevate Oral Care
Category: prescription | Type: HUMAN PRESCRIPTION DRUG LABEL
Date: 20250923

ACTIVE INGREDIENTS: SODIUM FLUORIDE 1.1 g/100 g
INACTIVE INGREDIENTS: WATER; HYDRATED SILICA; DIMETHICONE PEG-8 ADIPATE; SUCRALOSE; XANTHAN GUM; GLYCERIN; XYLITOL; SODIUM HYDROXIDE; TITANIUM DIOXIDE

Allday 5000 1.1% Sodium Fluoride Toothpaste, Spearmint